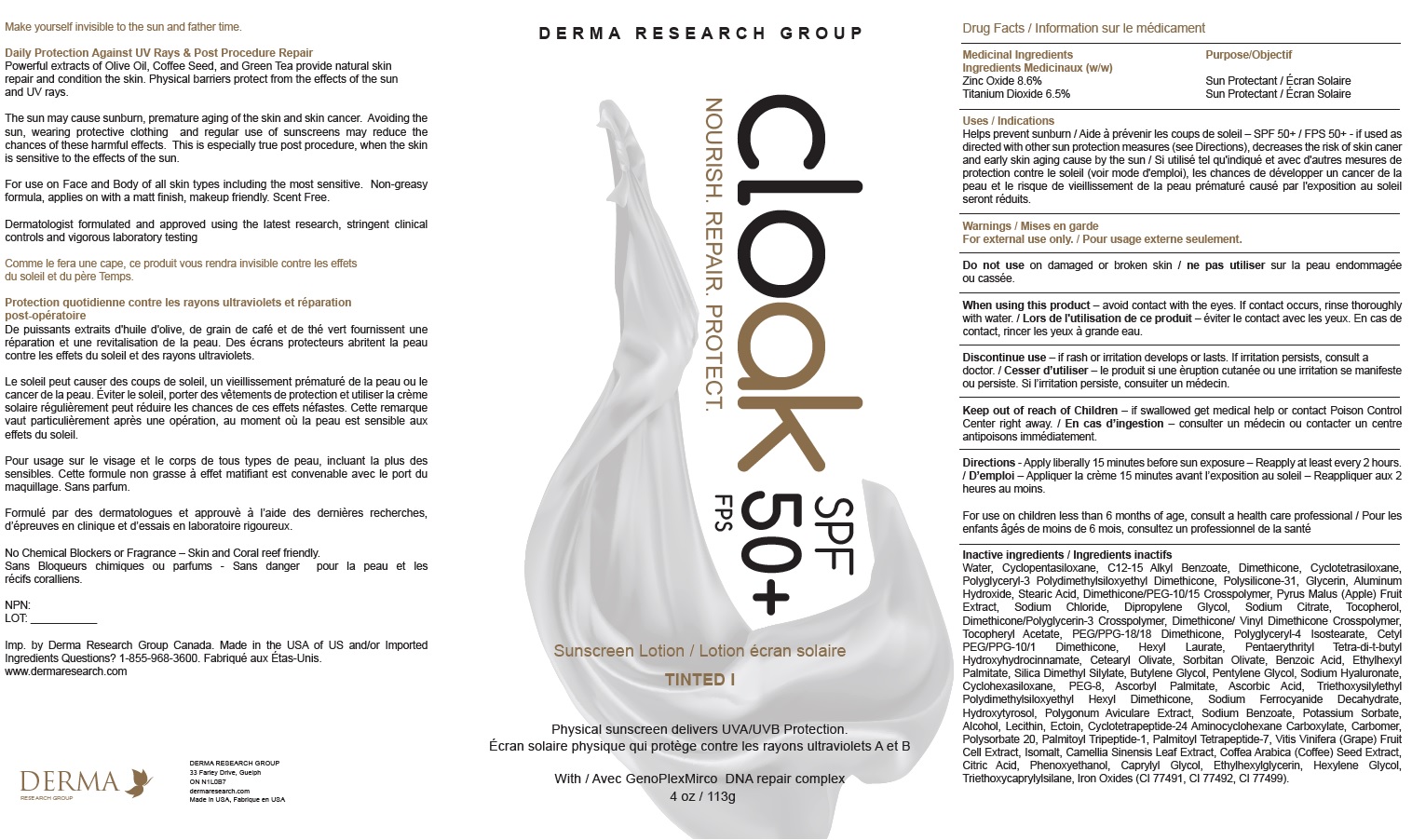 DRUG LABEL: Cloak SPF 50
NDC: 82038-001 | Form: CREAM
Manufacturer: Derma Research Group Inc.
Category: otc | Type: HUMAN OTC DRUG LABEL
Date: 20210924

ACTIVE INGREDIENTS: ZINC OXIDE 86 mg/1 g; TITANIUM DIOXIDE 65 mg/1 g
INACTIVE INGREDIENTS: ALUMINUM HYDROXIDE; DIMETHICONE/VINYL DIMETHICONE CROSSPOLYMER (SOFT PARTICLE); WATER; ALKYL (C12-15) BENZOATE; DIMETHICONE; .ALPHA.-TOCOPHEROL ACETATE; CETEARYL OLIVATE; SORBITAN OLIVATE; SILICA DIMETHYL SILYLATE; PENTYLENE GLYCOL; ASCORBIC ACID; LECITHIN, SOYBEAN; CYCLOTETRAPEPTIDE-24 AMINOCYCLOHEXANE CARBOXYLATE; SODIUM CHLORIDE; DIPROPYLENE GLYCOL; SODIUM CITRATE; DIMETHICONE/PEG-10/15 CROSSPOLYMER; CYCLOMETHICONE 4; POLYGLYCERYL-3 POLYDIMETHYLSILOXYETHYL DIMETHICONE (4000 MPA.S); STEARIC ACID; SODIUM BENZOATE; POTASSIUM SORBATE; ALCOHOL; POLYSORBATE 20; PALMITOYL TETRAPEPTIDE-7; GREEN TEA LEAF; ARABICA COFFEE BEAN; FERRIC OXIDE YELLOW; ISOMALT; CITRIC ACID MONOHYDRATE; PHENOXYETHANOL; TRIETHOXYCAPRYLYLSILANE; FERROSOFERRIC OXIDE; POLYGONUM AVICULARE TOP; PALMITOYL TRIPEPTIDE-1; HEXYLENE GLYCOL; CETYL PEG/PPG-10/1 DIMETHICONE (HLB 2); POLYGLYCERYL-4 ISOSTEARATE; PENTAERYTHRITOL TETRAKIS(3-(3,5-DI-TERT-BUTYL-4-HYDROXYPHENYL)PROPIONATE); BUTYLENE GLYCOL; HYALURONATE SODIUM; ASCORBYL PALMITATE; SODIUM FERROCYANIDE DECAHYDRATE; ECTOINE; CARBOXYPOLYMETHYLENE; WINE GRAPE; BENZOIC ACID; TOCOPHEROL; APPLE; FERRIC OXIDE RED; ETHYLHEXYL PALMITATE; CYCLOMETHICONE 6; GLYCERIN; CYCLOMETHICONE 5; HEXYL LAURATE; POLYETHYLENE GLYCOL 400; TRIETHOXYSILYLETHYL POLYDIMETHYLSILOXYETHYL HEXYL DIMETHICONE; HYDROXYTYROSOL; CAPRYLYL GLYCOL; ETHYLHEXYLGLYCERIN; PEG/PPG-18/18 DIMETHICONE

Drug Facts

ACTIVE INGREDIENT

Medicinal Ingredients
Zinc Oxide 8.6%
Titanium Dioxide 6.5%

Purpose:

Sun Protectant

Uses / Indications
Helps prevent sunburn / if used as directed with other sun protection measures (see Directions), decreases the risk of skin caner

Warning:

For External Use Only.

Do not use on damaged or broken skin

When using this product – avoid contact with the eyes. If contact occurs, rinse thoroughly with water.

STOP USE

Discontinue use – if rash or irritation develops or lasts. If irritation persists, consult a doctor.

Keep out of reach of Children – if swallowed get medical help or contact Poison Control Center right away.

DOSAGE AND ADMINISTRATION

Directions - Apply liberally 15 minutes before sun exposure – Reapply at least every 2 hours.

OTHER SAFETY INFORMATION

For use on children less than 6 months of age, consult a health care professional.

Inactive ingredients
Water, Cyclopentasiloxane, C12-15 Alkyl Benzoate, Dimethicone, Cyclotetrasiloxane,
Polyglyceryl-3 Polydimethylsiloxyethyl Dimethicone, Polysilicone-31, Glycerin, Aluminum
Hydroxide, Stearic Acid, Dimethicone/PEG-10/15 Crosspolymer, Pyrus Malus (Apple) Fruit
Extract, Sodium Chloride, Dipropylene Glycol, Sodium Citrate, Tocopherol,
Dimethicone/Polyglycerin-3 Crosspolymer, Dimethicone/ Vinyl Dimethicone Crosspolymer,
Tocopheryl Acetate, PEG/PPG-18/18 Dimethicone, Polyglyceryl-4 Isostearate, Cetyl
PEG/PPG-10/1 Dimethicone, Hexyl Laurate, Pentaerythrityl Tetra-di-t-butyl
Hydroxyhydrocinnamate, Cetearyl Olivate, Sorbitan Olivate, Benzoic Acid, Ethylhexyl
Palmitate, Silica Dimethyl Silylate, Butylene Glycol, Pentylene Glycol, Sodium Hyaluronate,
Cyclohexasiloxane, PEG-8, Ascorbyl Palmitate, Ascorbic Acid, Triethoxysilylethyl
Polydimethylsiloxyethyl Hexyl Dimethicone, Sodium Ferrocyanide Decahydrate,
Hydroxytyrosol, Polygonum Aviculare Extract, Sodium Benzoate, Potassium Sorbate,
Alcohol, Lecithin, Ectoin, Cyclotetrapeptide-24 Aminocyclohexane Carboxylate, Carbomer,
Polysorbate 20, Palmitoyl Tripeptide-1, Palmitoyl Tetrapeptide-7, Vitis Vinifera (Grape) Fruit
Cell Extract, Isomalt, Camellia Sinensis Leaf Extract, Coffea Arabica (Coffee) Seed Extract,
Citric Acid, Phenoxyethanol, Caprylyl Glycol, Ethylhexylglycerin, Hexylene Glycol,
Triethoxycaprylylsilane, Iron Oxides (CI 77491, CI 77492, CI 77499).

PACKAGE LABEL

Imp. by Derma Research Group Canada. Made in the USA of US and/or Imported
Ingredients Questions? 1-855-968-3600.
www.dermaresearch.com